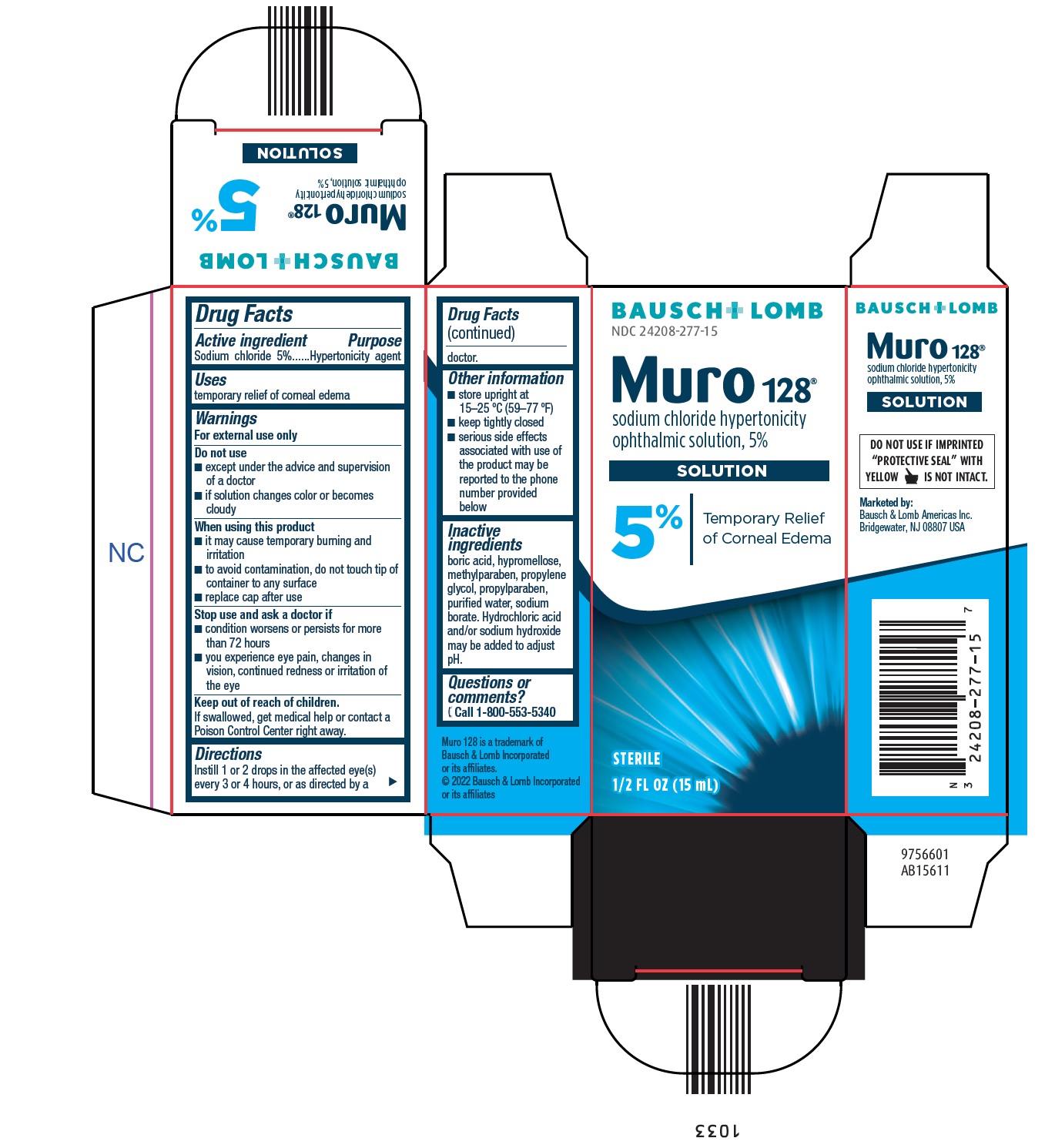 DRUG LABEL: Muro 128
NDC: 24208-277 | Form: SOLUTION
Manufacturer: Bausch & Lomb Incorporated
Category: otc | Type: HUMAN OTC DRUG LABEL
Date: 20240925

ACTIVE INGREDIENTS: SODIUM CHLORIDE 50 mg/1 mL
INACTIVE INGREDIENTS: BORIC ACID; HYPROMELLOSE, UNSPECIFIED; PROPYLENE GLYCOL; WATER; SODIUM BORATE; METHYLPARABEN; PROPYLPARABEN; HYDROCHLORIC ACID; SODIUM HYDROXIDE

Muro 128

Active ingredient

Sodium chloride 5%

Purpose

Hypertonicity agent

Uses

temporary relief of corneal edema

Warnings

For external use only

Do not use

- except under the advice and supervision of a doctor
- if solution changes color or becomes cloudy

When using this product

- it may cause temporary burning and irritation
- to avoid contamination, do not touch tip of container to any surface
- replace cap after use

Stop use and ask a doctor if

- condition worsens or persists for more than 72 hours
- you experience eye pain, changes in vision, continued redness or irritation of the eye

Keep out of reach of children.

If swallowed, get medical help or contact a Poison Control Center right away.

Directions

- Instill 1 or 2 drops in the affected eye(s) every 3 or 4 hours, or as directed by a doctor.

Other information

- store upright at 15–25 °C (59–77 °F)
- keep tightly closed
- serious side effects associated with use of the product may be reported to the phone number provided below

Inactive ingredients

boric acid, hypromellose, methylparaben, propylene glycol, propylparaben, purified water, sodium borate. Hydrochloric acid and/or sodium hydroxide may be added to adjust pH.

Questions or comments?

[telephone icon] Call 1-800-553-5340

Muro 128 is a trademark of Bausch & Lomb Incorporated or its affiliates.

© 2022 Bausch & Lomb Incorporated or its affiliates

Marketed by:

Bausch & Lomb Americas Inc.

Bridgewater, NJ 08807 USA

9756601

AB15611

Package/Label Principal Display Panel – Muro 128 15 mL

BAUSCH + LOMB

NDC 24208-277-15

Muro 128®

sodium chloride hypertonicity

ophthalmic solution, 5%

SOLUTION

5%

Temporary Relief

of Corneal Edema

STERILE

1/2 FL OZ (15 mL)